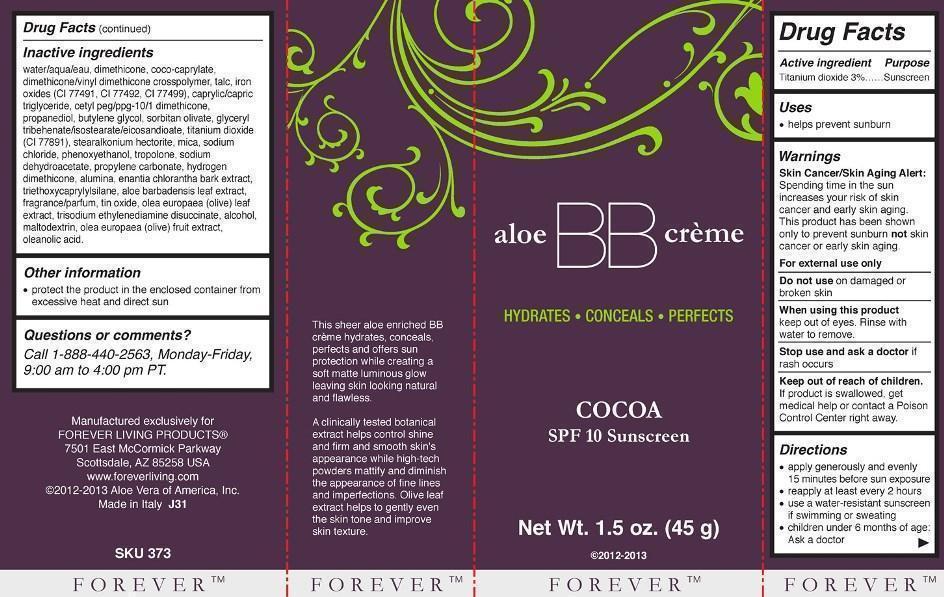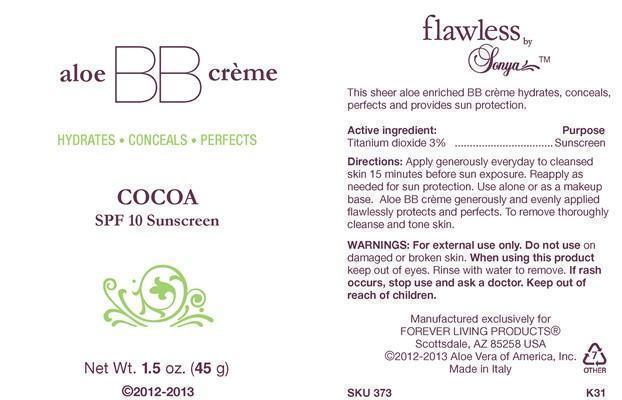 DRUG LABEL: Flawless by Sonya Aloe BB Creme
NDC: 11697-373 | Form: CREAM
Manufacturer: Aloe Vera of America, Inc.
Category: otc | Type: HUMAN OTC DRUG LABEL
Date: 20140113

ACTIVE INGREDIENTS: TITANIUM DIOXIDE 1.3500 g/45.0000 g
INACTIVE INGREDIENTS: WATER; DIMETHICONE; COCO-CAPRYLATE; DIMETHICONE/VINYL DIMETHICONE CROSSPOLYMER (SOFT PARTICLE); TALC; FERRIC OXIDE RED; FERRIC OXIDE YELLOW; FERROSOFERRIC OXIDE; MEDIUM-CHAIN TRIGLYCERIDES; CETYL PEG/PPG-10/1 DIMETHICONE (HLB 3); PROPANEDIOL; BUTYLENE GLYCOL; SORBITAN OLIVATE; GLYCERYL TRIBEHENATE/ISOSTEARATE/EICOSANDIOATE; STEARALKONIUM HECTORITE; MICA; SODIUM CHLORIDE; PHENOXYETHANOL; TROPOLONE; SODIUM DEHYDROACETATE; PROPYLENE CARBONATE; METHICONE (20 CST); ALUMINUM OXIDE; ANNICKIA CHLORANTHA BARK; TRIETHOXYCAPRYLYLSILANE; ALOE VERA LEAF; STANNIC OXIDE; OLEA EUROPAEA BARK; TRISODIUM ETHYLENEDIAMINE DISUCCINATE; ALCOHOL; MALTODEXTRIN; BLACK OLIVE; OLEANOLIC ACID

Drug Facts for Flawless by Sonya Aloe BB Creme - Cocoa 373

Active Ingredient | Purpose
Titanium dioxide 3%..................................... | Sunscreen

Uses

- helps prevent sunburn

Warnings

Skin Cancer/Skin Aging Alert: Spending time in the sun increases your risk of skin cancer and early skin aging. This product has been shown only to prevent sunburn not skin cancer or early skin aging.

For external use only

Do not use on damaged or broken skin

When using this product keep out of eyes. Rinse with water to remove.

Stop use and ask a doctor if rash occurs

Keep out of reach of children.

If product is swallowed, get medical help or contact a Poison Control Center right away.

Directions

- apply generously and evenly 15 minutes before sun exposure
- reapply at least every 2 hours
- use a water-resistant sunscreen if swimming or sweating
- children under 6 months of age: Ask a doctor

Inactive Ingredients

water/aqua/eau, dimethicone, coco-caprylate, dimethicone/vinyl dimethicone crosspolymer, talc, iron oxides (CI 77491, CI 77492, CI 77499), caprylic/capric triglyceride, cetyl peg/ppg-10/1 dimethicone, propanediol, butylene glycol, sorbitan olivate, glyceryl tribehante/isostearate/eicosandioate, titanium dioxide (CI 77891), stearalkonium hectorite, mica, sodium chloride, phenoxyethanol, tropolone, sodium dehydroacetate, propylene carbonate, hydrogen dimethicone, alumina, enantia chlorantha bark extract, triethoxycaprylylsilane, aloe barbadensis leaf extract, fragrance/parfum, tin oxide, olea europaea (olive) leaf extract, trisodium ethylenediamine disuccinate, alcohol, maltodextrin, olea europaea (olive) fruit extract, oleanolic acid.

Other Information

- protect the product in the enclosed container from excessive heat and direct sun

Questions or comments?

Call 1-888-440-2563, Monday-Friday, 9:00 am to 4:00 pm PT.